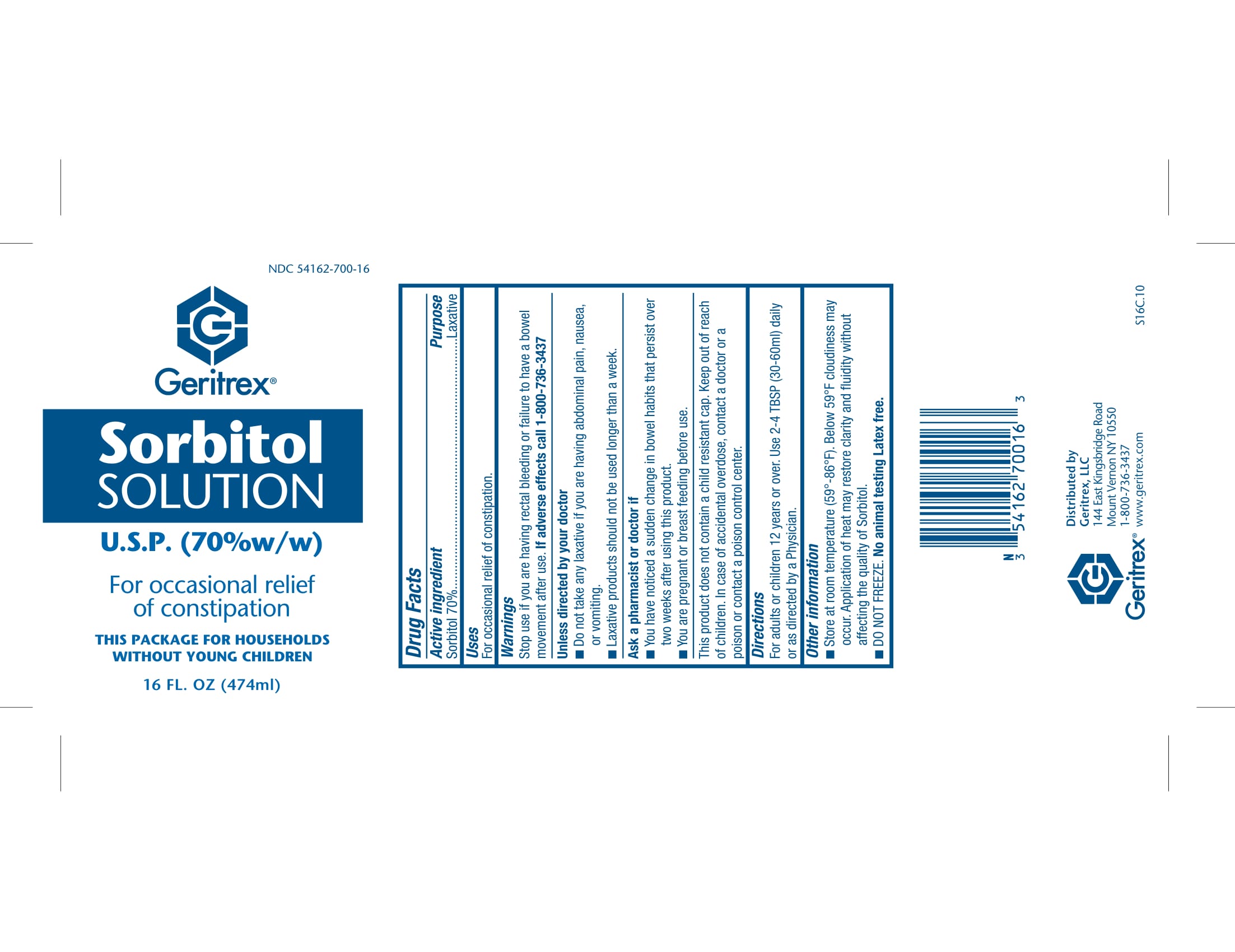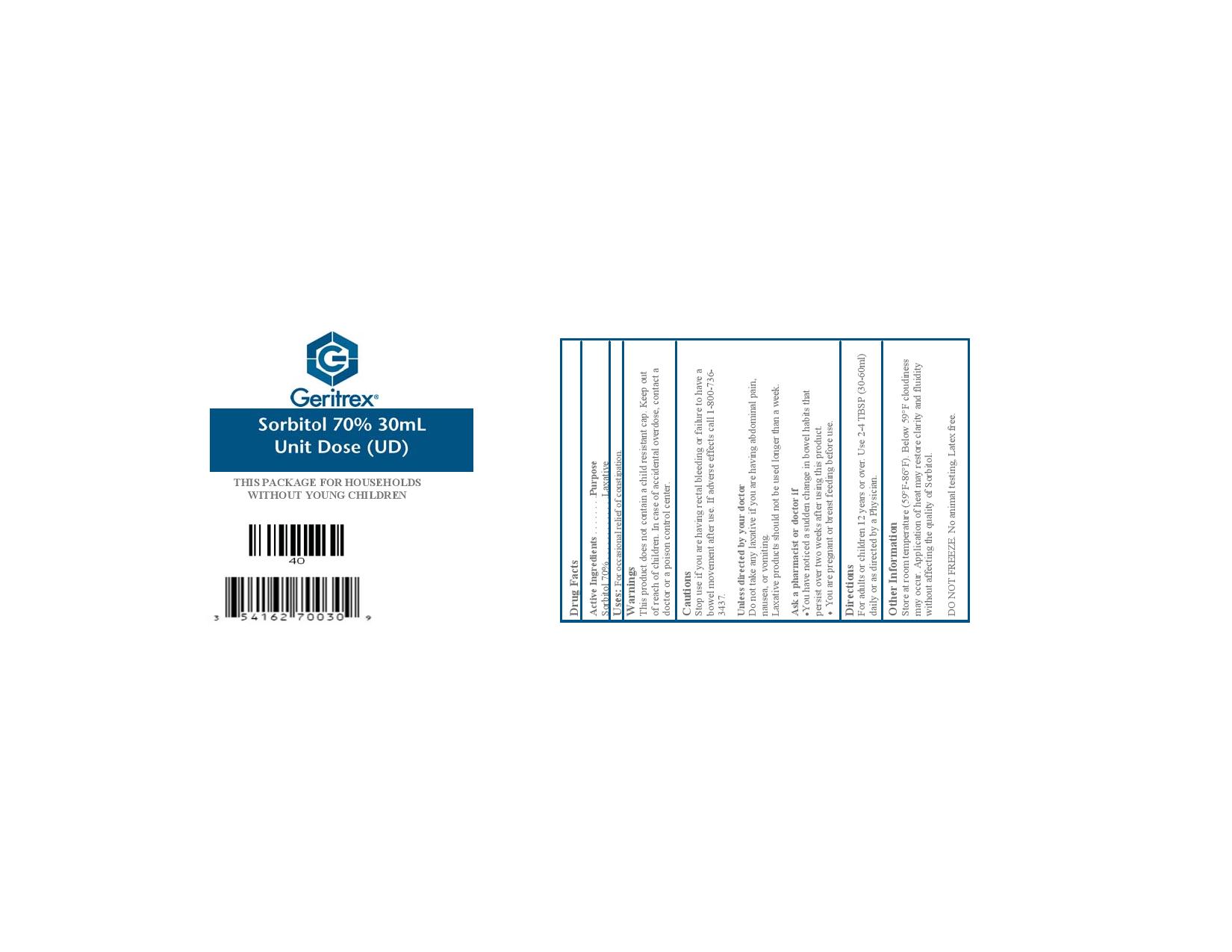 DRUG LABEL: Sorbitol
NDC: 54162-700 | Form: SOLUTION
Manufacturer: Geritrex LLC
Category: otc | Type: HUMAN OTC DRUG LABEL
Date: 20180117

ACTIVE INGREDIENTS: SORBITOL 258.2 g/474 mL
INACTIVE INGREDIENTS: WATER

Sorbitol Solution

Active Ingredients

Active Ingredients . . . . . . . .Purpose
Sorbitol 70% . . . . . . . . . . . . .Laxative

Uses

For occasional relief of constipation.

Directions

For adults or children 12 years or over. Use 2-4 TBSP (30-60ml)
daily or as directed by a Physician.

DOSAGE AND ADMINISTRATION

Use 2-4 TBSP (30-60ml)
daily or as directed by a Physician.

Warnings

This product does not contain a child resistant cap. Keep out
of reach of children. In case of accidental overdose, contact a
doctor or a poison control center.
Cautions
Stop use if you are having rectal bleeding or failure to have a
bowel movement after use. If adverse effects call 1-800-736-
3437
Unless directed by your doctor
Do not take any laxative if you are having abdominal pain,
nausea, or vomiting.
Laxative products should not be used longer than a week.
Ask a pharmacist or doctor if
• You have noticed a sudden change in bowel habits that
persist over two weeks after using this product.
• You are pregnant or breast feeding before use.

INACTIVE INGREDIENT

Water

STORAGE AND HANDLING

Store at room temperature (59°F-86°F). Below 59°F cloudiness
may occur. Application of heat may restore clarity and fluidity
without affecting the quality of Sorbitol.
DO NOT FREEZE.

Keep out of reach of children. In case of accidental overdose, contact a
doctor or a poison control center.